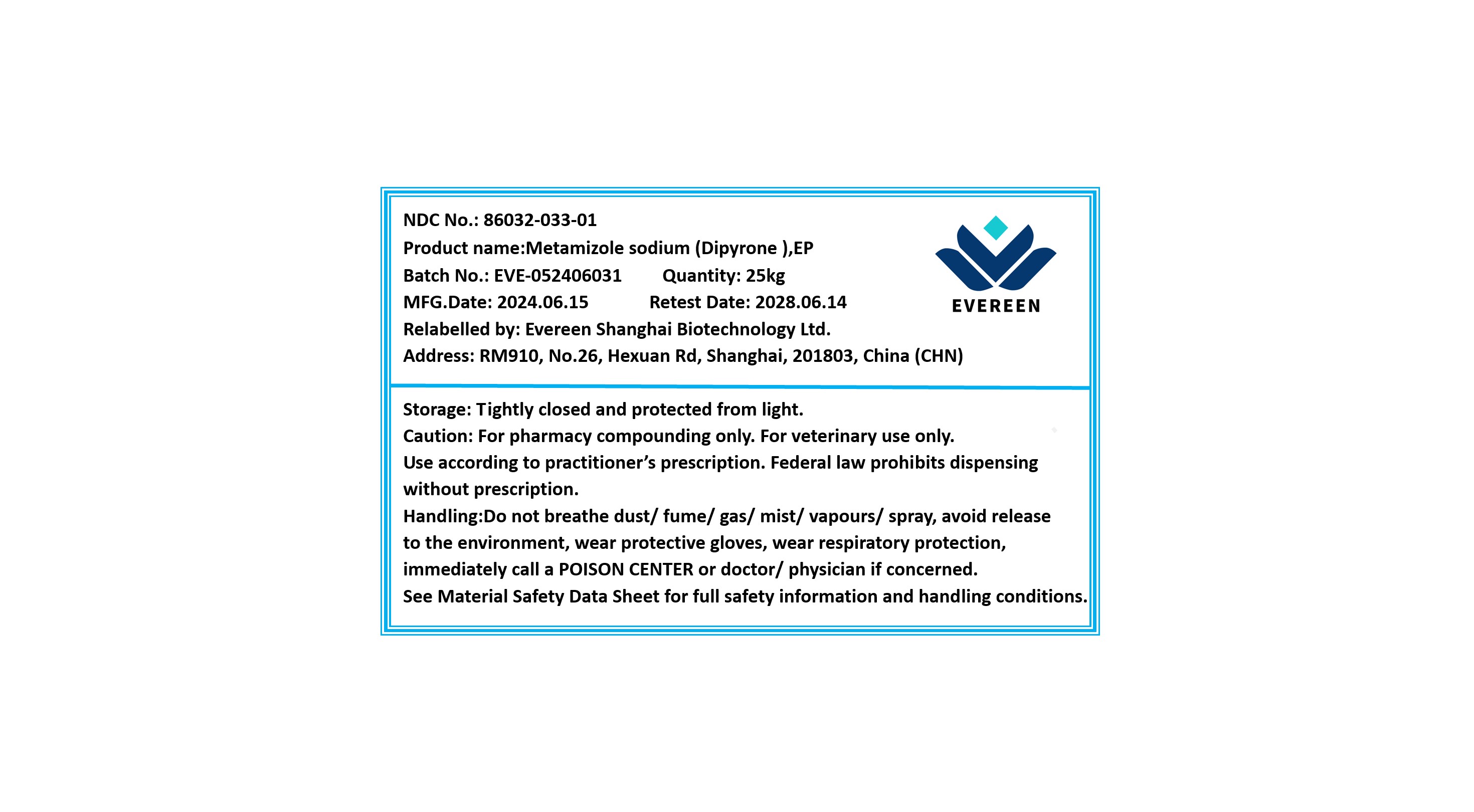 DRUG LABEL: Metamizole sodium
NDC: 86032-033 | Form: POWDER
Manufacturer: Evereen Shanghai Biotechnology Ltd.
Category: other | Type: BULK INGREDIENT - ANIMAL DRUG
Date: 20250106

ACTIVE INGREDIENTS: METAMIZOLE SODIUM 1 kg/1 kg

Metamizole sodium